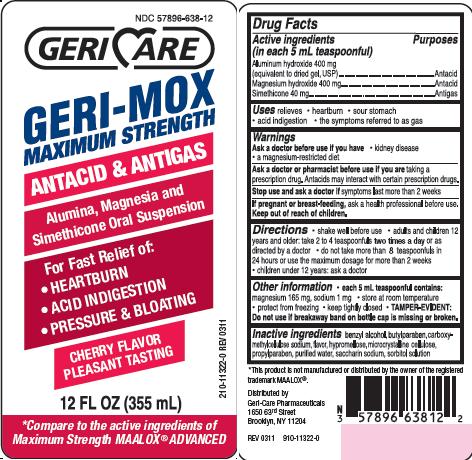 DRUG LABEL: GERI-MOX MAX CHERRY
NDC: 57896-638 | Form: SUSPENSION
Manufacturer: Geri-Care Pharmaceuticals, Corp
Category: otc | Type: HUMAN OTC DRUG LABEL
Date: 20251119

ACTIVE INGREDIENTS: ALUMINUM HYDROXIDE 400 mg/5 mL; MAGNESIUM HYDROXIDE 400 mg/5 mL; DIMETHICONE 40 mg/5 mL
INACTIVE INGREDIENTS: BENZYL ALCOHOL; BUTYLPARABEN; CARBOXYMETHYLCELLULOSE SODIUM; HYPROMELLOSES; CELLULOSE, MICROCRYSTALLINE; PROPYLPARABEN; WATER; SACCHARIN SODIUM; SORBITOL

geri-mox chry

Active ingredients (in each 5 mL teaspoonful)

Aluminum hydroxide 400 mg (equivalent to dried gel, USP)
Magnesium hydroxide 400 mg
Simethicone 40mg

Purposes

Antacid
Antigas

Uses

relieves

- heartburn
- sour stomach
- acid indigestion
- the symptoms referred to as gas

Warnings

Ask a doctor before use if you have
• kidney disease
• a magnesium-restricted diet
Ask a doctor or pharmacist before use if you are taking a prescription drug.
Antacids may interact with certain prescription drugs.
Stop use and ask a doctor if symptoms last more than 2 weeks
If pregnant or breast-feeding, ask a health professional before use.

Keep out of reach of children.

Directions

• shake well before use
• adults and children 12 years and older: take 2 to 4 teaspoonfuls two times a day, or as directed by a doctor
• do not take more than 8 teaspoonfuls in 24 hours or use the maximum dosage for more than 2 weeks
• children under 12 years: ask a doctor

Other information

• each 5 mL teaspoonful contains: magnesium 165 mg, sodium 1 mg
• store at room temperature

• protect from freezing
• keep tightly closed

• TAMPER-EVIDENT: Do not use if breakaway band on bottle cap is missing or broken.

Inactive ingredients

benzyl alcohol, butylparaben, carboxymethylcellulose sodium, flavor, hypromellose, microcrystalline cellulose, propylparaben, purified water, saccharin sodium, sorbitol solution

package Label

NDC 57896-638-12
GERICARE
GERI-MOX

MAXIMUM STRENGTH

antacid and antigas
Alumina, Magnesia and Simethicone Oral Suspension
For Fast Relief of:
HEARTBURN
ACID INDIGESTION
PRESSURE AND BLOATING

cherry flavor pleasant tasting
12 FL OZ (355 mL)

compare to the active ingredients of Maximum Strength MAALOX ADVANCED